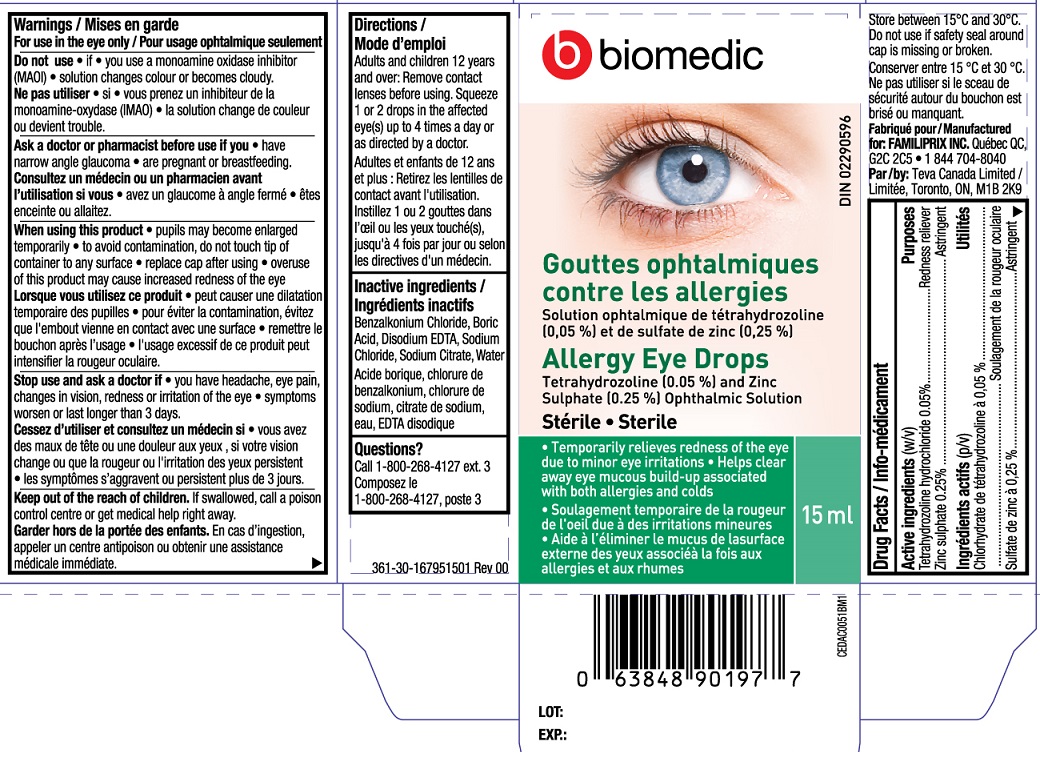 DRUG LABEL: Biomedic Allergy Eye Drops
NDC: 55651-013 | Form: SOLUTION/ DROPS
Manufacturer: K.C. Pharmaceuticals, Inc.
Category: otc | Type: HUMAN OTC DRUG LABEL
Date: 20251231

ACTIVE INGREDIENTS: ZINC SULFATE 0.25 g/100 mL; TETRAHYDROZOLINE 0.05 g/100 mL
INACTIVE INGREDIENTS: BENZALKONIUM CHLORIDE; BORIC ACID; EDETATE DISODIUM; SODIUM CITRATE; WATER; SODIUM CHLORIDE

Biomedic Allergy Eye Drops15 mL MFR